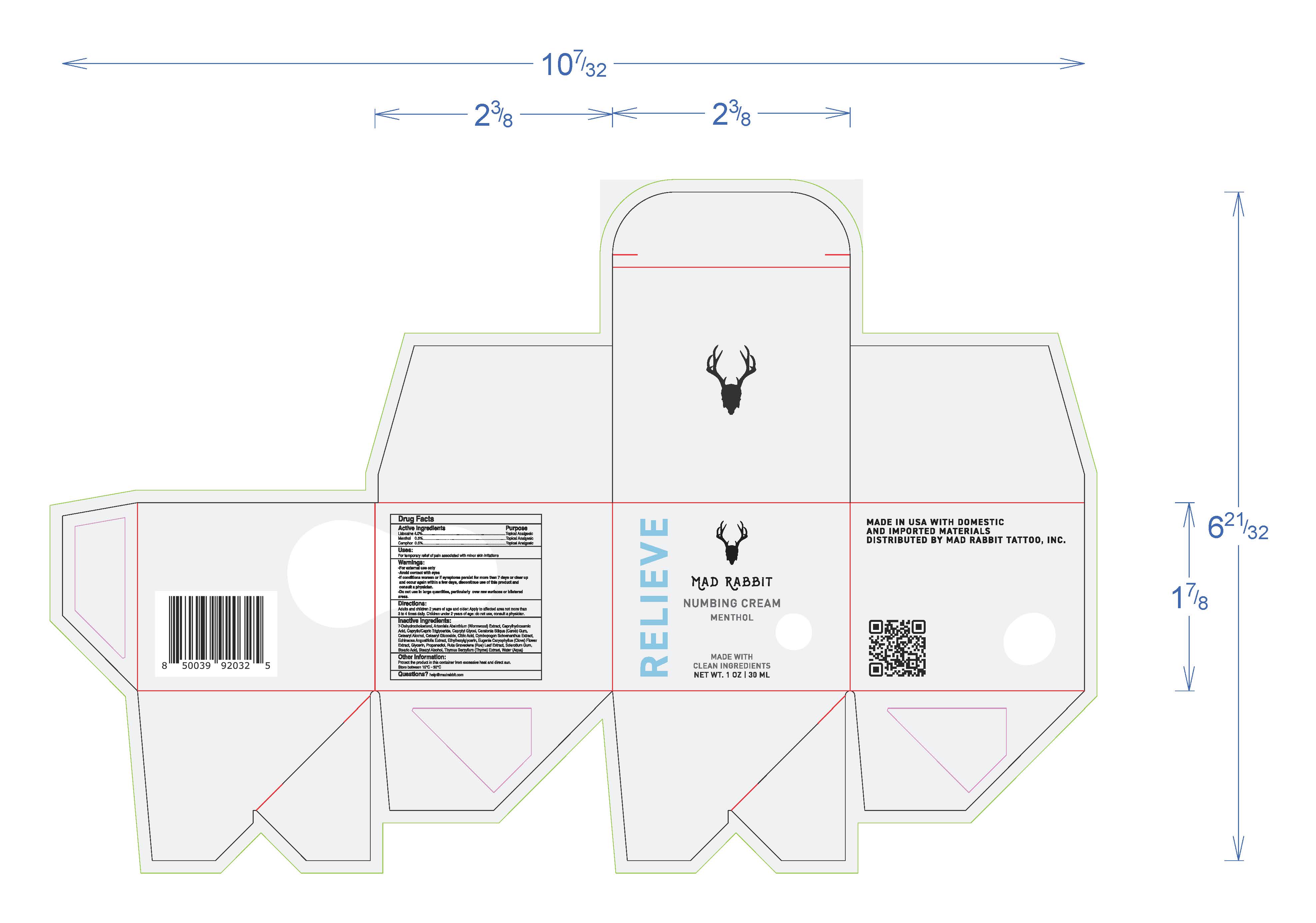 DRUG LABEL: Mad Rabbit Numbing Cream Menthol
NDC: 80396-020 | Form: CREAM
Manufacturer: MAD RABBIT TATTOO, INC.
Category: otc | Type: HUMAN OTC DRUG LABEL
Date: 20241204

ACTIVE INGREDIENTS: LIDOCAINE 4 g/1 mL; MENTHOL 0.5 g/1 mL; CAMPHOR (NATURAL) 0.5 g/1 mL
INACTIVE INGREDIENTS: 7-DEHYDROCHOLESTEROL; ARTEMISIA ABSINTHIUM WHOLE; CAPRYLHYDROXAMIC ACID; CAPRYLIC/CAPRIC/LAURIC TRIGLYCERIDE; CAPRYLYL GLYCOL; CERATONIA SILIQUA WHOLE; CETEARYL GLUCOSIDE; CITRIC ACID ACETATE; CYMBOPOGON SCHOENANTHUS WHOLE; ECHINACEA ANGUSTIFOLIA WHOLE; ETHYLHEXYLGLYCERIN; GLYCERIN; PROPANEDIOL; RUTA GRAVEOLENS WHOLE; STEARIC ACID; STEARYL ALCOHOL; THYMUS SERPYLLUM WHOLE; WATER

Mad Rabbit Numbing Cream Menthol

Active Ingredients

Lidocaine 4.0%

Menthol 0.5%

Camphor 0.5%

Purpose

Topical Analgesic

Uses

For temporary relief of pain associated with minor skin irritants

Warnings

For external use only
Avoid contact with eyes
If conditions worsen or if symptoms persist for more than 7 days or clear up and occur again within a few days, discontinue use of this product and consult a physician
Do not use in large quantities, particulary over raw surfaces or blistered areas

Directions

Adults and children 2 years of age and older: Apply to affected area not more than 3 to 4 times daily. Children under 2 years of age: do not use, consult a physician.

Keep out of reach of children.

Inactive Ingredients

7-Dehydrocholesterol, Artemisia Absinthium (Wormwood) Extract, Caprylhydroxamic Acid, Caprylic/Capric Triglyceride, Caprylyl Glycol, Ceratonia Siliqua (Carob) Gum, Cetearyl Alcohol, Cetearyl Glucoside, Citric Acid, Cymbopogon Schoenanthus Extract, Echninacea Angustifolia Extract, Ethylhexylglycerin, Eugenia Caryophyllus (Clove) Flower Extract, Glycerin, Propanediol, Ruta Graveolens (Rue) Leaf Extract, Sclerotium Gum, Stearic Acid, Stearyl Alcohol, Thymus Serpyllum (Thyme) Extract, Water (Aqua)

Other Information:

Protect the product in this container from excessive heat and direct sun. Store between 15°C-30°C

Questions or comments?

help@madrabbit.com